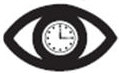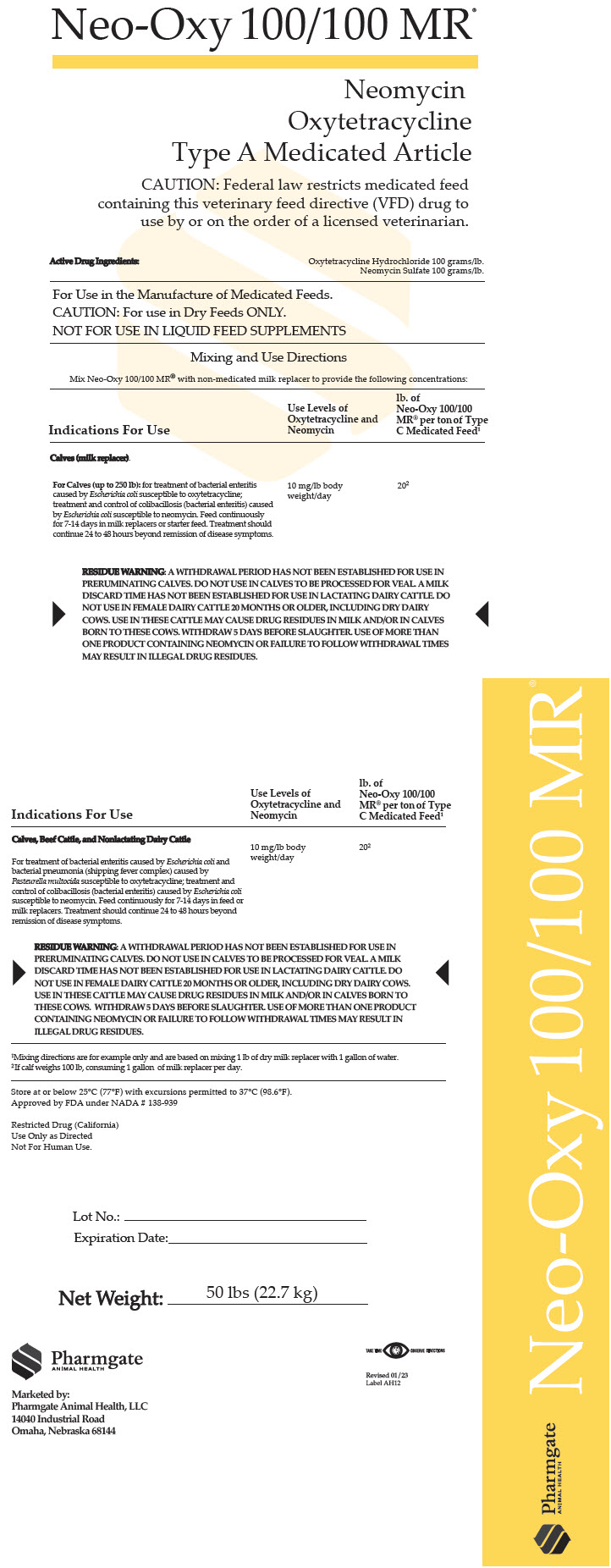 DRUG LABEL: Neo-Oxy 100/100 MR
NDC: 51429-010 | Form: POWDER
Manufacturer: Pharmgate Animal Health
Category: animal | Type: VFD TYPE A MEDICATED ARTICLE ANIMAL DRUG LABEL
Date: 20260107

ACTIVE INGREDIENTS: Oxytetracycline Hydrochloride 220 g/1 kg; Neomycin Sulfate 220 g/1 kg

Neo-Oxy 100/100 MR®

Neomycin
Oxytetracycline
Type A Medicated Article

CAUTION: Federal law restricts medicated feed containing this veterinary feed directive (VFD) drug to use by or on the order of a licensed veterinarian.

DESCRIPTION

Active Drug Ingredients:
Oxytetracycline Hydrochloride 100 grams/lb.
Neomycin Sulfate 100 grams/lb.

For Use in the Manufacture of Medicated Feeds

CAUTION: For Use in Dry Feeds ONLY.

NOT FOR USE IN LIQUID FEED SUPPLEMENTS

VETERINARY INDICATIONS

Mixing and Use Directions

Mix Neo-Oxy 100/100 MR® with non-medicated milk replacer to provide the following concentrations:

INDICATIONS FOR USE

Use Level of Oxytetracycline and Neomycin

lbs. of Neo-Oxy 100/100 MR per ton of Type C Medicated Feed [Mixing directions are for example only and are based on mixing 1 lb of dry milk replacer with 1 gallon of water.]

Calves (milk replacer)

For Calves (up to 250 lb): For treatment of bacterial enteritis caused by Escherichia coli susceptible to oxytetracycline; treatment and control of colibacillosis (bacterial enteritis) caused by Escherichia coli susceptible by neomycin. Feed continuously for 7-14 days in milk replacer or starter feed. Treatment should continue 24 to 48 hours beyond remission of disease symptoms.

10 mg/lb body weight/day

20 [If calf weighs 100 lb, consuming 1 gallon of milk replacer per day.]

RESIDUE WARNING: A WITHDRAWAL PERIOD HAS NOT BEEN ESTABLISHED FOR USE IN PRERUMINATING CALVES. DO NOT USE IN CALVES TO BE PROCESSED FOR VEAL. A MILK DISCARD TIME HAS NOT BEEN ESTABLISHED FOR USE IN LACTATING DAIRY CATTLE. DO NOT USE IN FEMALE DAIRY CATTLE 20 MONTHS OR OLDER, INCLUDING DRY DAIRY COWS. USE IN THESE CATTLE MAY CAUSE DRUG RESIDUES IN MILK AND/OR IN CALVES BORN TO THESE COWS. WITHDRAW 5 DAYS BEFORE SLAUGHTER. USE OF MORE THAN ONE PRODUCT CONTAINING NEOMYCIN OR FAILURE TO FOLLOW WITHDRAWAL TIMES MAY RESULT IN ILLEGAL DRUG RESIDUES

Calves, Beef Cattle, and Nonlactating Dairy Cattle

For treatment of bacterial enteritis caused by Escherichia coli and bacterial pneumonia (shipping fever complex) caused by Pasteurella multocida susceptible to oxytetracycline; treatment and control of colibacillosis (bacterial enteritis) caused by Escherichia coli susceptible by neomycin. Feed continuously for 7-14 days in feed or milk replacers. Treatment should continue 24 to 48 hours beyond remission of disease symptoms.

10 mg/lb body weight/day

20

RESIDUE WARNINGS: A WITHDRAWAL PERIOD HAS NOT BEEN ESTABLISHED FOR USE IN PRERUMINATING CALVES. DO NOT USE IN CALVES TO BE PROCESSED FOR VEAL. A MILK DISCARD TIME HAS NOT BEEN ESTABLISHED FOR USE IN LACTATING DAIRY CATTLE. DO NOT USE IN FEMALE DAIRY CATTLE 20 MONTHS OR OLDER, INCLUDING DRY DAIRY COWS. USE IN THESE CATTLE MAY CAUSE DRUG RESIDUES IN MILK AND/OR IN CALVES BORN TO THESE COWS. WITHDRAW 5 DAYS BEFORE SLAUGHTER. USE OF MORE THAN ONE PRODUCT CONTAINING NEOMYCIN OR FAILURE TO FOLLOW WITHDRAWAL TIMES MAY RESULT IN ILLEGAL DRUG RESIDUES

Store at or below 25°C (77°F) with excursions permitted to 37°C (98.6°F).
Approved by FDA under NADA # 138-939

Restricted Drug (California)
Use Only as Directed.
Not For Human Use.

Net Weight 50 lbs (22.7 kg)

Marketed by:
Pharmgate Animal Health, LLC
14040 Industrial Road
Omaha, NE 68144

Take TimeObserve Directions

PRINCIPAL DISPLAY PANEL - 22.7 kg Drum Label

Neo-Oxy 100/100 MR®

Neomycin
Oxytetracycline
Type A Medicated Article

CAUTION: Federal law restricts medicated feed
containing this veterinary feed directive (VFD) drug to
use by or on the order of a licensed veterinarian.